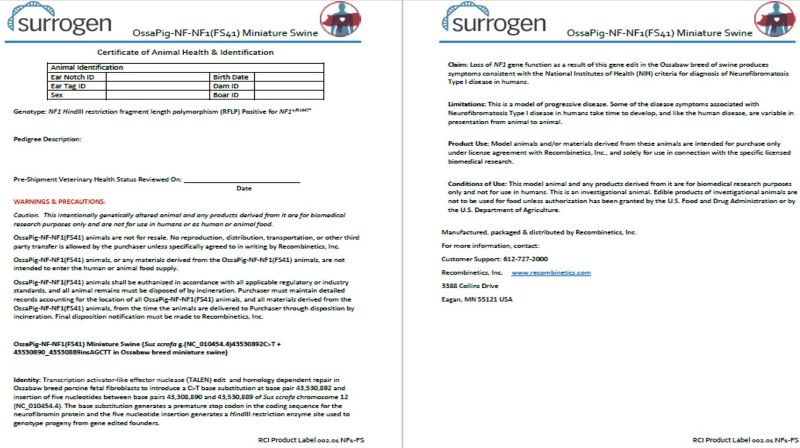 DRUG LABEL: OssaPig-NF-NF1(FS41) Miniature Swine
NDC: 86086-002 | Form: NOT APPLICABLE
Manufacturer: Recombinetics, Inc.
Category: other | Type: INTENTIONAL ANIMAL GENOMIC ALTERATION LABEL
Date: 20240724

ACTIVE INGREDIENTS: SUS SCROFA G.(NC_010454.4)43530892C>T + 43530890_43530889insAGCTT IN OSSABAW MINIATURE SWINE 1 [arb'U]/1 [arb'U]

OssaPig-NF-NF1(FS41) Miniature Swine

STATEMENT OF IDENTITY

Identity: Transcription activator-like effector nuclease (TALEN) edit and homology dependent repair in Ossabaw breed porcine fetal fibroblasts to introduce a C>T base substitution at base pair 43,530,892 and insertion of five nucleotides between base pairs 43,308,890 and 43,530,889 of Sus scrofa chromosome 12 (NC_010454.4). The base substitution generates a premature stop codon in the coding sequence for the neurofibromin protein and the five nucleotide insertion generates a HindIII restriction enzyme site used to genotype progeny from gene edited founders.

HEALTH CLAIM

Claim: Loss of NF1 gene function as a result of this gene edit in the Ossabaw breed of swine produces symptoms consistent with the National Institutes of Health (NIH) criteria for diagnosis of Neurofibromatosis Type I disease in humans.

CONTRAINDICATIONS

Limitations: This is a model of progressive disease. Some of the disease symptoms associated with Neurofibromatosis Type I disease in humans take time to develop, and like the human disease, are variable in presentation from animal to animal.

INDICATIONS AND USAGE

Product Use: Model animals and/or materials derived from these animals are intended for purchase only under license agreement with Recombinetics, Inc., and solely for use in connection with the specific licensed biomedical research.

INDICATIONS AND USAGE

Conditions of Use: This model animal and any products derived from it are for biomedical research purposes only and not for use in humans. This is an investigational animal. Edible products of investigational animals are not to be used for food unless authorization has been granted by the U.S. Food and Drug Administration or by the U.S. Department of Agriculture.

WARNINGS AND PRECAUTIONS

Caution. This intentionally genetically altered animal and any products derived from it are for biomedical research purposes only and are not for use in humans or as human or animal food.
OssaPig-NF-NF1(FS41) animals are not for resale. No reproduction, distribution, transportation, or other third party transfer is allowed by the purchaser unless specifically agreed to in writing by Recombinetics, Inc.
OssaPig-NF-NF1(FS41) animals, or any materials derived from the OssaPig-NF-NF1(FS41) animals, are not intended to enter the human or animal food supply.
OssaPig-NF-NF1(FS41) animals shall be euthanized in accordance with all applicable regulatory or industry standards, and all animal remains must be disposed of by incineration. Purchaser must maintain detailed records accounting for the location of all OssaPig-NF-NF1(FS41) animals, and all materials derived from the OssaPig-NF-NF1(FS41) animals, from the time the animals are delivered to Purchaser through disposition by incineration. Final disposition notification must be made to Recombinetics, Inc.